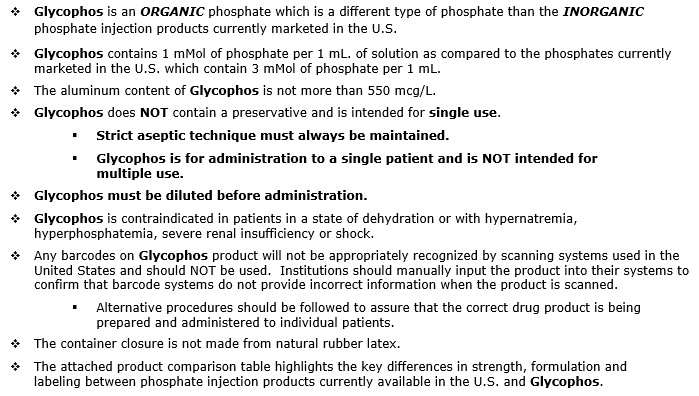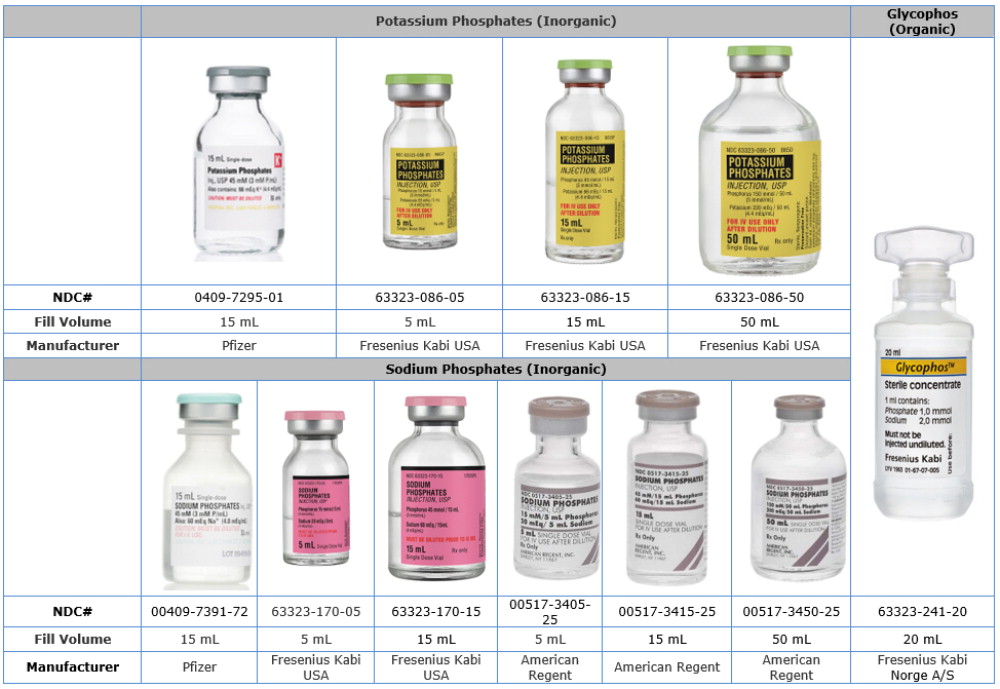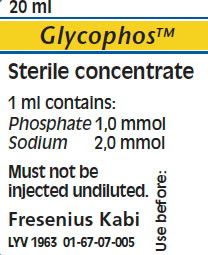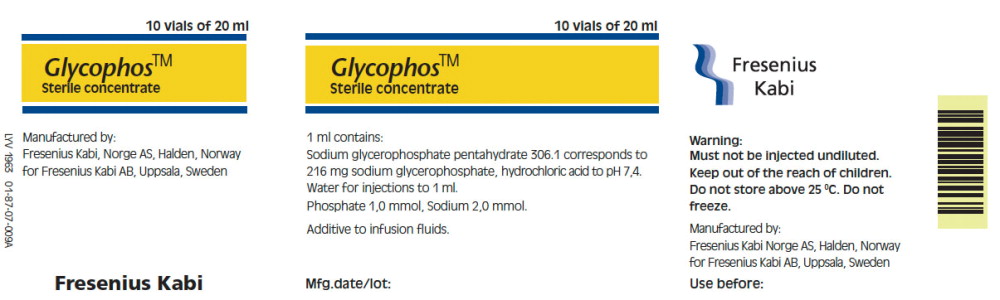 DRUG LABEL: Glycophos
NDC: 63323-241 | Form: INJECTION, SOLUTION
Manufacturer: Fresenius Kabi USA, LLC
Category: prescription | Type: Human Prescription Drug Label
Date: 20221207

ACTIVE INGREDIENTS: SODIUM GLYCEROPHOSPHATE ANHYDROUS 216 mg/1 mL
INACTIVE INGREDIENTS: HYDROCHLORIC ACID

Glycophos

HEALTH CARE PROVIDER LETTER

IMPORTANT PRESCRIBING INFORMATION
October 30, 2017

Subject: Temporary importation of Glycophos to address drug shortage issues

Dear Healthcare Professional,
Due to the critical shortage of phosphate injection in the U.S. market, Fresenius Kabi USA, LLC (Fresenius Kabi USA) is coordinating with the U.S. Food and Drug Administration (FDA) to provide an alternative treatment option during this critical shortage period. Fresenius Kabi USA has initiated temporary importation of a GlycophosTM 20 mL Injection Single Dose Plastic Vial into the U.S. market. This product is marketed in Europe, and is manufactured in the Fresenius Kabi Norway plant.

At this time, no other entity except Fresenius Kabi USA is authorized by the FDA to import or distribute GlycophosTM 20 mL Injection Single Dose Plastic Vial in the U.S. FDA has not approved Fresenius Kabi's GlycophosTM in the United States.

Effective immediately, and during this temporary period, Fresenius Kabi USA will offer the following presentation of phosphate injection:

Glycophos 20 mL
Sterile Concentrate
Single Dose Plastic Vial
Chemical Name | Sodium Glycerophosphate
Phosphate Concentration | 1 mMol per mL.
Type of Phosphate | Organic
Sodium | 2 mEq per mL.
Fill Volume | 20 mL.
Description | Single Dose Plastic Vial
Manufacturer | Fresenius Kabi Norge A/S

The vial and carton labels will display the text used when marketing the product in English speaking countries.

It is important to note that there are some key differences in the formulation and labeling
between the current U.S. marketed phosphate injection products and Glycophos that you need to be aware of:
Refer to the Glycophos package insert for full prescribing information
This communication and product information is available on the Fresenius Kabi USA web site http://products.fresenius-kabi.us/product-323.html as well as on the FDA Drug Shortage web site. http://www.fda.gov/Drugs/DrugSafety/DrugShortages/default.htm.

To report adverse events or quality problems experienced with the use of this product, call Fresenius Kabi USA Vigilance or Medical Affairs at 1-800-551-7176, Monday – Friday, between the hours of 8 a.m. and 5 p.m. (CST), or e-mail adverse.events.USA@fresenius-kabi.com or productcomplaint.USA@fresenius-kabi.com.

Fresenius Kabi USA CONTACT NUMBERS: Please use the following contact numbers as appropriate:

Reason To Call | Department | Number
ADE Reporting | Vigilance Department | 1-800-551-7176
Clinical/Technical Info. Or Product Complaint | Medical Affairs Department | 1-800-551-7176
Product Availability & Ordering | Customer Service Department | 1-888-386-1300

Adverse reactions or quality problems experienced with the use of this product may be reported to the FDA’s MedWatch Adverse Event Reporting program either online, by regular mail or by fax.

- Complete and submit the report Online: www.fda.gov/medwatch/report.htm
- Regular Mail or Fax: Download form www.fda.gov/medwatch/getforms.htm or call 1-800-332-1088 to request a reporting form, then complete and return to the address on the pre-addressed form, or submit by fax to 1-800-FDA-0178 (1-800-332-0178).

Sincerely,
Melanie Power-Burns
Vice President, Quality and Compliance
Key Differences between U.S. Marketed Phosphate Injection Products and Glycophos

Current U.S. Marketed Inorganic Phosphate Injection, USP | Glycophos | What does this mean to you, as a Healthcare Professional?
Indications and contraindications: see package insert | Indications and contraindications: see package insert | Glycophos is indicated in adult patients and infants as a supplement in intravenous nutrition to meet the requirements of phosphate. Glycophos is contraindicated in patients in a state of dehydration or with hypernatremia, hyperphosphatemia, severe renal insufficiency or shock.
Sodium Phosphates and Potassium Phosphates contain 3 mMol of phosphate per mL. | Glycophos contains 1 mMol of phosphate per mL. | Glycophos contains 20 mLs in each plastic vial for a total concentration of 20 mMols of phosphate per vial. Glycophos must be diluted before administration.
Sodium Phosphates and Potassium Phosphates are INORGANIC PHOSPHATE. | Glycophos is an ORGANIC PHOSPHATE. | Organic phosphates tend to be more calcium compatible^1. This means:; - At higher concentrations, solutions of calcium and phosphate may exist together without precipitating into an insoluble salt complex. - In high pH solutions (admixtures above pH 6.0), organic phosphate is less likely to precipitate.
Barcode on container label | No unit of use barcode | Any barcodes on Glycophos product will not be appropriately recognized by scanning systems used in the United States and should NOT be used. Institutions should manually input the product into their systems and to confirm that barcode systems do not provide incorrect information when the product is scanned.
For questions regarding Glycophos in the United States, please contact
Fresenius Kabi USA Medical Affairs at 1-800-551-7176 Option 4,
Monday – Friday, between the hours of 8 a.m. and 5 p.m. (CST), or e-mail nutrition.medinfo.USA@fresenius-kabi.com.

1. Data on file.
Comparison Table of U.S. Phosphate Injection Products to Glycophos

Product Name | Potassium Phosphates | Sodium Phosphates | Glycophos
Chemical Name | Potassium Phosphate | Sodium Phosphate | Sodium Glycerophosphate
Phosphate Concentration | 3 mMol per mL | 3 mMol per mL | 1 mMol per mL
Type of Phosphate | Inorganic | Inorganic | Organic
Sodium | Does not contain | 4 mEq per mL | 2 mEq per mL
Potassium | 4.4 mEq per mL | Does not contain | Does not contain
Fill Volume | 5 mL, 15 mL, 50 mL | 5 mL, 15 mL, 50 mL | 20 mL
Description | Single Dose Vial | Single Dose Vial | Single Dose Plastic Vial
Companies | Fresenius Kabi USA, Pfizer | American Regent, Fresenius Kabi USA, Pfizer | Fresenius Kabi Norge A/S

Phosphate Label Product Comparison Table

MEDICATION GUIDE

1. QUALITATIVE AND QUANTITATIVE COMPOSITION

1 ml of Glycophos contains

Active ingredient Quantity

Sodium glycerophosphate pentahydrate 306.1 mg*

*Corresponds to 216 mg sodium glycerophosphate

The active ingredient in 1 ml of Glycophos correspond to

Phosphate 1 mmol

Sodium 2 mmol

For excipients, see 5.1

PRODUCT PROPERTIES

• Osmolality: 2760 mosm/kg water

• pH: 7.4

2. PHARMACEUTICAL FORM

Concentrate for solution for infusion.

3. CLINICAL PARTICULARS

3.1 Therapeutic indications

Glycophos is indicated in adult patients and infants as a supplement in intravenous nutrition to meet the requirements of phosphate.

3.2 Posology and method of administration

Glycophos must not be given undiluted.

Adults:

The recommended dosage is individual. The recommended daily dosage of phosphate during intravenous nutrition would normally be 10-20 mmol. This can be met by using 10-20 ml of Glycophos added to the infusion solution or to the admixture for which compatibility has been proved.

Infants:

The recommended dosage is individual. The recommended dose for infants and neonates is 1.0-1.5 mmol/Kg body weight/day.

3.3 Contra-indications

Glycophos should not be given to patients in a state of dehydration or with hypernatraemia, hyperphosphataemia, severe renal insufficiency or shock.

3.4 Special warnings and special precautions for use

Glycophos should be used with caution in patients with impaired renal function. The phosphate status of all patients should be monitored regularly.

Glycophos must not be given undiluted.

3.5 Interaction with other medicaments and other forms of interaction

No interactions with other drugs have been observed, but a moderate fall in serum phosphate can be seen during carbohydrate infusions.

3.6 Pregnancy and lactation

Animal reproduction studies or clinical investigations during pregnancy have not been carried out with Glycophos. However, the requirements of phosphate in a pregnant woman are slightly increased compared to non-pregnant women.

No adverse events are to be expected when Glycophos is administered during pregnancy.

3.7 Effects on ability to drive and use machines

No effects on the ability to drive and use machines are to be expected.

3.8 Undesirable effects

No adverse effects related to glycerophosphate have been reported.

3.9 Overdose

No adverse effects of an overdose have been reported. Most patients in need of intravenous nutrition have an increased capacity to handle glycerophosphate. See also 3.3 "Contra-indications".

4. PHARMACOLOGICAL PROPERTIES

4.1 Pharmacodynamic properties

Glycerophosphate is a metabolic intermediate in fat metabolism and any pharmacodynamic effects other than maintaining the normal metabolic pathways are unlikely.

4.2 Pharmacokinetic properties

To become available it is necessary for the phosphate group to be hydrolysed from the glycerophosphate molecule. The hydrolysis occurs maximally at a plasma concentration of >0.7 mmol/l. Assuming that all hydrolysis of glycerophosphate takes place in plasma, about 12-15 mmol of sodium glycerophosphate will be hydrolysed each day in individuals with normal serum alkaline phosphatase.

No pharmacokinetical data is available for infants, however with the recommended dosage hyperphosphataemia is unlikely.

4.3 Preclinical safety data

Preclinical safety studies on Glycophos demonstrated good tolerance.

5. PHARMACEUTICAL PARTICULARS

5.1 List of excipients

Hydrochloric acid

Water for Injections

5.2 Incompatibilities

Glycophos may only be added to or mixed with other medicinal products for which compatibility has been documented. See 5.6.

5.3 Shelf life

3 years

5.4 Special precautions for storage

Do not store above 25°C. Do not freeze.

5.5 Nature and contents of container

Polypropylene vial.

Pack size: 10 x 20 ml

5.6 Instructions for use/handling

Glycophos must not be given undiluted.

Compatibility

Additions should be made aseptically.

Up to 120 ml of Glycophos and 48 mmol of calcium (as CaCl2) can be added to 1000 ml Vamin Glucose, Vamin 9 Electrolyte Free, Vamin 14, Vamin 14 Electrolyte Free, Vamin 18 Electrolyte Free and Vaminolact.

Up to 10 ml of Glycophos and 10 mmol of calcium (as CaCl2) can be added to 1000 ml Glucose 50 mg/ml.

Up to 20 ml of Glycophos and 20 mmol of calcium (as CaCl2) can be added to 1000 ml Glucose 200 mg/ml.

Up to 60 mmol of Glycophos and 24 mmol of calcium (as CaCl2) can be added to 1000 ml Glucose 500 mg/ml.

Infusion time

The infusion time should not be less than 8 hours.

Stability

When additions are made to an infusion solution, the infusion should be completed within 24 hours from preparation to prevent microbiological contamination. The left over contents of opened bottles/vials/ampoules should be discarded and not kept for later use.

PACKAGE LABEL

PACKAGE LABEL - PRINCIPAL DISPLAY PANEL - Glycophos 20 mL Vial Label

20 ml

Glycophos™

Sterile concentrate

PACKAGE LABEL - PRINCIPAL DISPLAY PANEL - Glycophos 20 mL Vial Carton Panel

10 vials of 20 ml

Glycophos™

Sterile concentrate